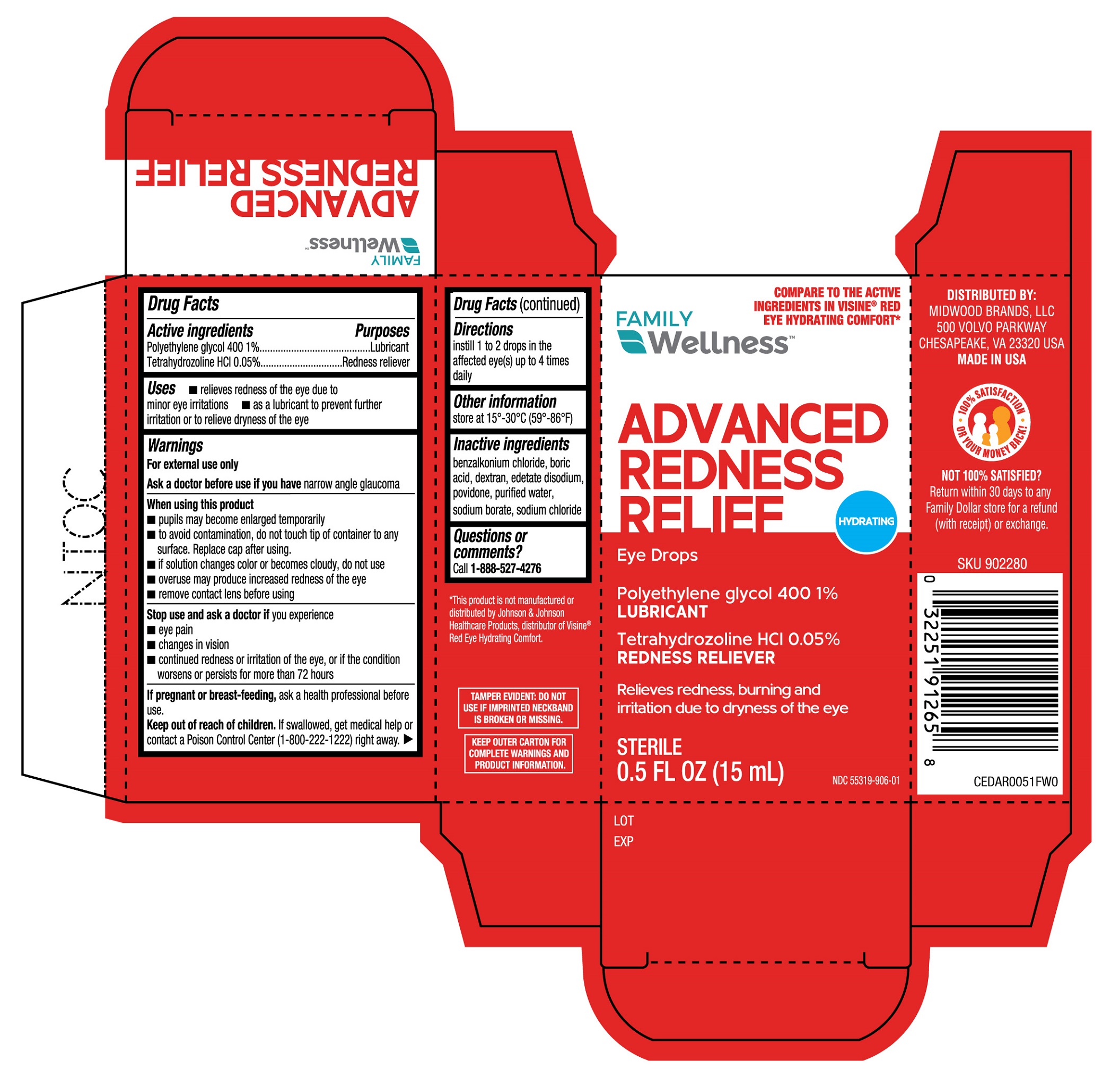 DRUG LABEL: Family Wellness Advanced Redness Relief Eye Drops
NDC: 55319-906 | Form: SOLUTION/ DROPS
Manufacturer: Family Dollar Services, Inc.
Category: otc | Type: HUMAN OTC DRUG LABEL
Date: 20251230

ACTIVE INGREDIENTS: POLYETHYLENE GLYCOL 400 1 g/100 mL; TETRAHYDROZOLINE HYDROCHLORIDE 0.05 g/100 mL
INACTIVE INGREDIENTS: DEXTRAN 70; BORIC ACID; SODIUM CHLORIDE; WATER; SODIUM BORATE; POVIDONE; BENZALKONIUM CHLORIDE; EDETATE DISODIUM

Family Wellness Advanced Redness Relief 15mL (PLD)

Active ingredients

Polyethylene glycol 400 1%

Tetrahydrozoline HCl 0.05%

Purposes

Lubricant

Redness reliever

Uses

- relieves redness of the eye due to minor eye irritations
- as a lubricant to prevent further irritation or to relieve dryness of the eye

Warnings

For external use only

Ask a doctor before use if you have

narrow angle glaucoma

When using this product

- pupils may become enlarged temporarily
- to avoid contamination, do not touch tip of container to any surface. Replace cap after using.
- if solution changes color or becomes cloudy, do not use
- overuse may produce increased redness of the eye
- remove contact lens before using

Stop use and ask a doctor if

you experience

- eye pain
- changes in vision
- continued redness or irritation of the eye, or if the condition worsens or persists for more than 72 hours

If pregnant or breast-feeding,

ask a health professional before use.

Keep out of reach of children.

If swallowed, get medical help or contact a Poison Control Center (1-800-222-1222) right away.

Directions

instill 1 or 2 drops in the affected eye(s) up to 4 times daily

Other information

store at 15°-30°C (59°-86°F)

Inactive ingredients

benzalkonium chloride, boric acid, dextran, edetate disodium, povidone, purified water, sodium borate, sodium chloride

Questions or comments?

Call 1-888-527-4276